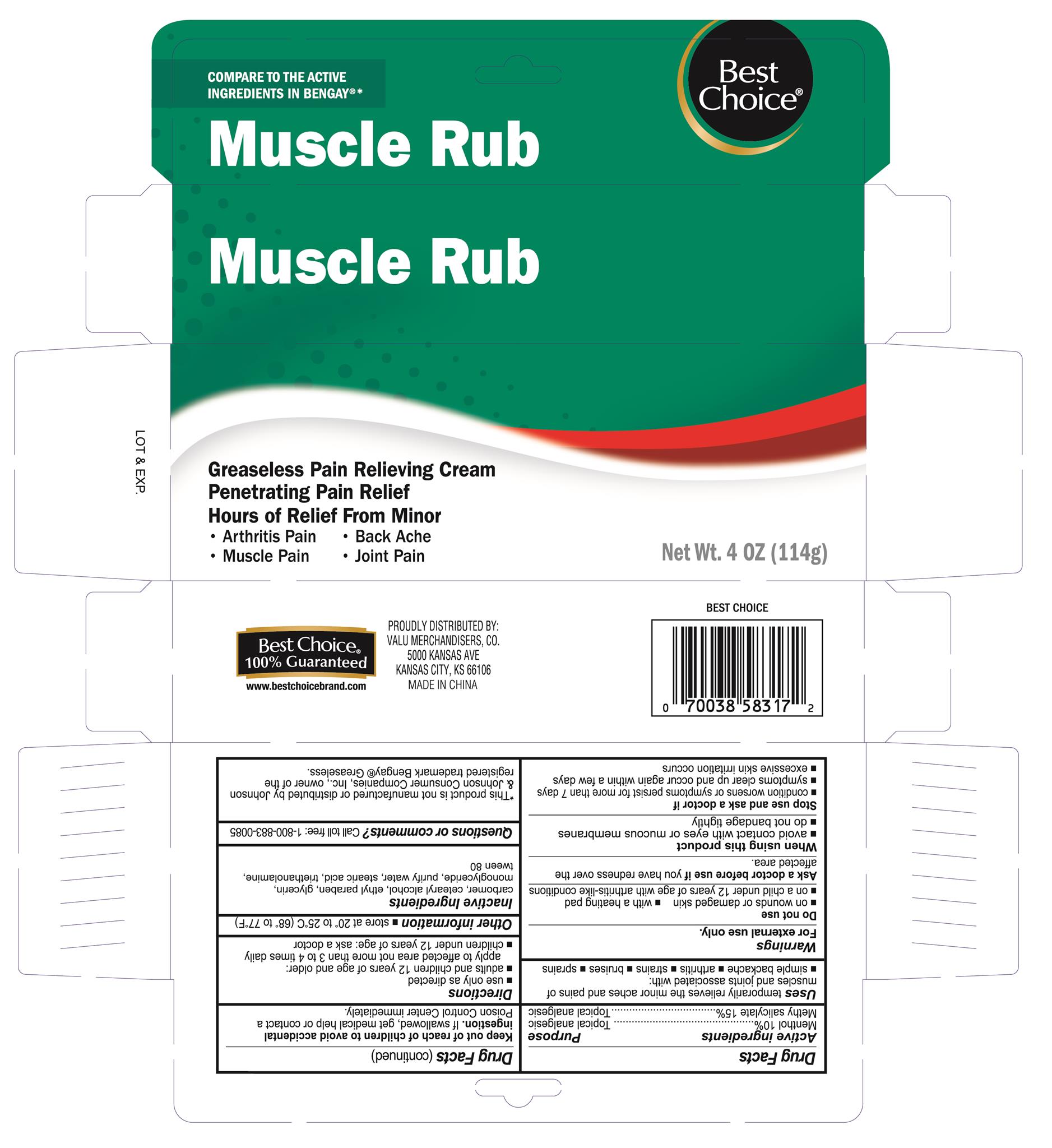 DRUG LABEL: Muscle and Joint Pain Relief
NDC: 63941-317 | Form: CREAM
Manufacturer: Valu Merchandisers, Co.
Category: otc | Type: HUMAN OTC DRUG LABEL
Date: 20230208

ACTIVE INGREDIENTS: MENTHOL 10 g/100 g; METHYL SALICYLATE 15 g/100 g
INACTIVE INGREDIENTS: CARBOXYPOLYMETHYLENE; CETYL ALCOHOL; GLYCERIN; GLYCERYL 1-STEARATE; ETHYLPARABEN; CUPRIC BIS(TRIETHANOLAMINE); WATER; STEARIC ACID; POLYSORBATE 80

Best Choice Muscle Rub Greaseless

Active ingredients

Menthol 10%

Methyl salicylate 15%

Uses

temporarily relieves the minor aches and pains of muscles and joints associated with:

- simple backache
- arthritis
- strains
- bruises
- sprains

Warnings

For external use only

Do not use

- on wounds or damaged skin
- with a heating pad
- on a child under 12 years of age with arthritis-like conditions

Ask a doctor before use if you have

redness over the affected area.

When using this product

- avoid contact with eyes or mucous membranes
- do not bandage tightly

Stop use and ask a doctor if

- condition worsens or symptoms persist for more than 7 days
- symptoms clear up and occur again within a few days
- excessive skin irritation occurs

Keep out of reach of children to avoid accidental ingestion.

If swallowed, get medical help or contact a Poison Control Center immediately.

Directions

- use only as directed
- adults and children 12 years of age and older: apply to affected area not more than 3 to 4 times daily
- children under 12 years of age: ask a doctor

Other information

- store at 20° to 25°C (68° to 77°F)

Inactive ingredients

carbomer, cetearyl alcohol, ethyl paraben, glycerin, monoglceride, purify water, stearic acid, triethanolamine, tween 80

Purpose

Topical analgesic

Topical analgesic

Package label

Best Choice Greaseless Muscle Rub